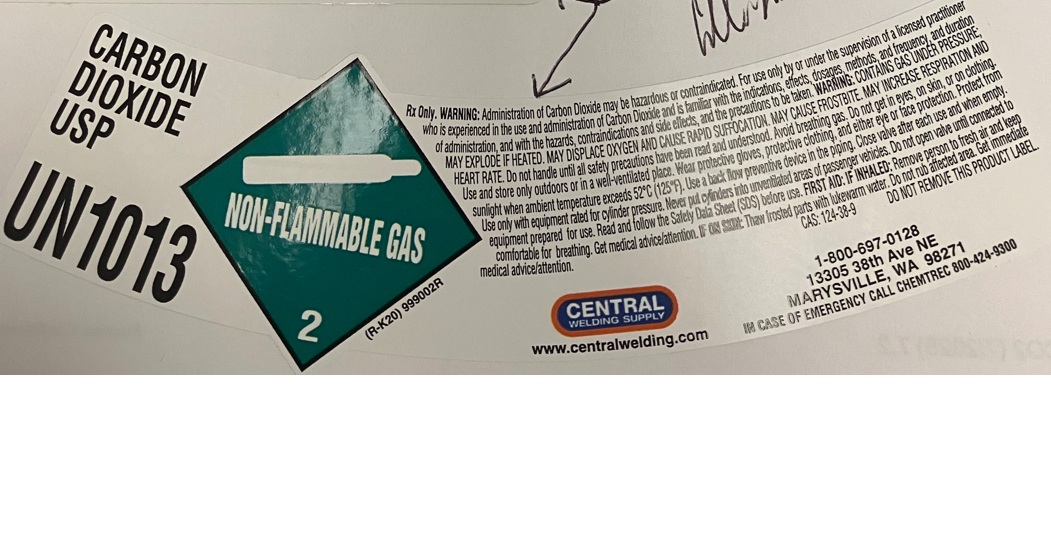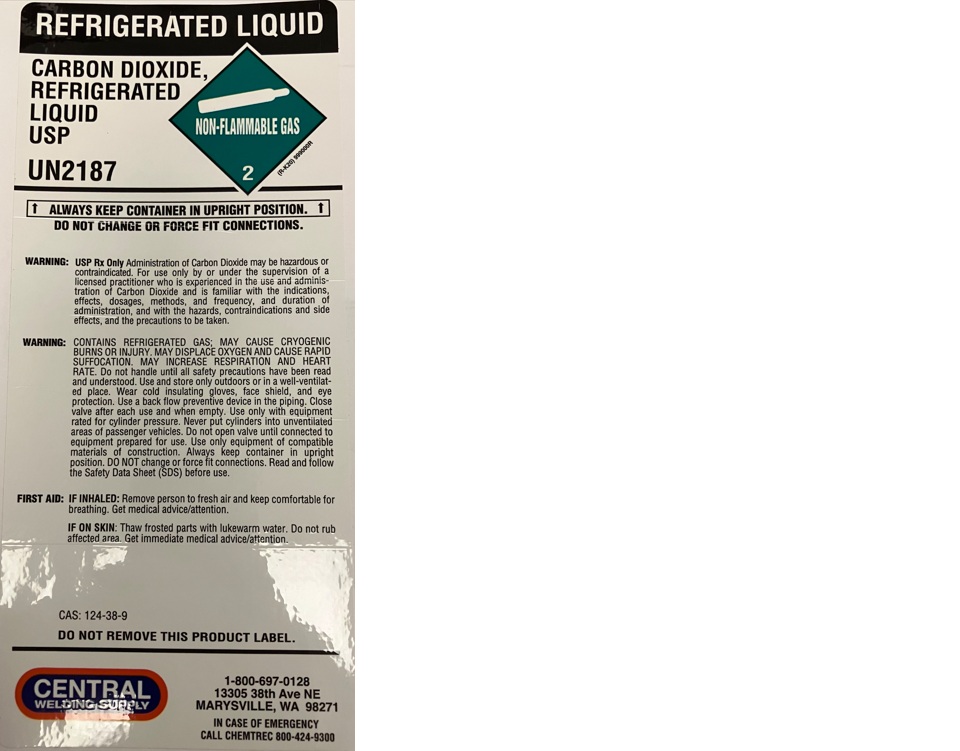 DRUG LABEL: Carbon Dioxide
NDC: 70151-030 | Form: GAS
Manufacturer: Central Welding Supply Company
Category: prescription | Type: HUMAN PRESCRIPTION DRUG LABEL
Date: 20260108

ACTIVE INGREDIENTS: CARBON DIOXIDE 992 mL/1 L

Carbon Dioxide

PACKAGE LABEL

CARBON DIOXIDE USP

UN1013

Rx Only. WARNING: Administration of Carbon Dioxide may be hazardous or contraindicated. For use only by or under the supervision of a licensed practitioner who is experienced in the use and administration of Carbon Dioxide and is familiar with the indications, effects, dosages, methods, and frequency, and duration of administration, and with the hazards, contraindications and side effects, and the precautions to be taken. WARNING: CONTAINS GAS UNDER PRESSURE; MAY EXPLODE IF HEATED. MAY DISPLACE OXYGEN AND CAUSE RAPID SUFFOCATION. MAY CAUSE FROSTBITE. MAY INCREASE RESPIRATION AND HEART RATE. Do not handle until all safety precautions have been read and understood. Avoid breathing gas. Do not get in eyes, on skin, or on clothing. Use and store only outdoors or in a well-ventilated place. Wear protective gloves, protective clothing, and either eye of face protection. Protect from sunlight when ambient temperature exceeds 52 C (125 F). Use a back flow preventive device in the piping. Close valve after each use and when empty. Use only with equipment rated for cylinder pressure. Never put cylinders into unventilated areas of passenger vehicles. Do not open valve until connected to equipment prepared for use. Read and follow the Safety Data Sheet (SDS) before use. FIRST AID: IF INHALED: Remove person to fresh air and keep comfortable for breathing. Get medical advice/attention. IF ON SKIN: Thaw frosted parts with lukewarm water. Do not rub affected area. Get immediate medical advice/attention.

CAS: 124-38-9 DO NOT REMOVE THIS PRODUCT LABEL.

CENTRAL WELDING SUPPLY

www.centralwelding.com

1-800-697-0128

13305 38th Ave NE

MARYSVILLE, WA 98271

IN CASE OF EMERGENCY CALL CHEMTREC 800-424-9300

PACKAGE LABEL

REFRIGERATED LIQUID

CARBON DIOXIDE, REFRIGERATED LIQUID USP

UN2187

ALWAYS KEEP CONTAINER IN UPRIGHT POSITION.

DO NOT CHANGE OR FORCE FIT CONNECTIONS.

WARNING: USP Rx Only Administration of Carbon Dioxide may be hazardous or contraindicated. For use only by or under the supervision of a licensed practitioner who is experienced in the use and administration of Carbon Dioxide and is familiar with the indications, effects, dosages, methods, and frequency, and duration of administration, and with the hazards, contraindications and side effects, and the precautions to be taken.

WARNING: CONTAINS REFRIGERATED GAS; MAY CAUSE CRYOGENIC BURNS OR INJURY. MAY DISPLACE OXYGEN AND CAUSE RAPID SUFFOCATION. MAY INCREASE RESPIRATION AND HEART RATE. Do not handle until all safety precautions have been read and understood. Use and store only outdoors or in a well-ventilated place. Wear cold insulting gloves, face shield, and eye protection. Use a back flow preventive device in the piping. Close valve after each use and when empty. Use only with equipment rated for cylinder pressure. Never put cylinder into unventilated areas of passenger vehicles. Do not open valve until connected to equipment prepared for use. Use only equipment of compatible materials of construction. Always keep container in upright position. DO NOT change or force fit connections. Read and follow the Safety Data Sheet (SDS) before use.

FIRST AID: IF INHALED: Remove person to fresh air and keep comfortable for breathing. Get medical advice/attention.

IF ON SKIN: Thaw frosted parts with lukewarm water. Do not rub affected area. Get immediate medical advice/attention.

CAS: 124-38-9

DO NOT REMOVE THIS PRODUCT LABEL.

CENTRAL WELDING SUPPLY

1-800-697-0128

13305 38th Ave NE

MARYSVILLE, WA 98271

IN CASE OF EMERGENCY CALL CHEMTREC 800-424-9300